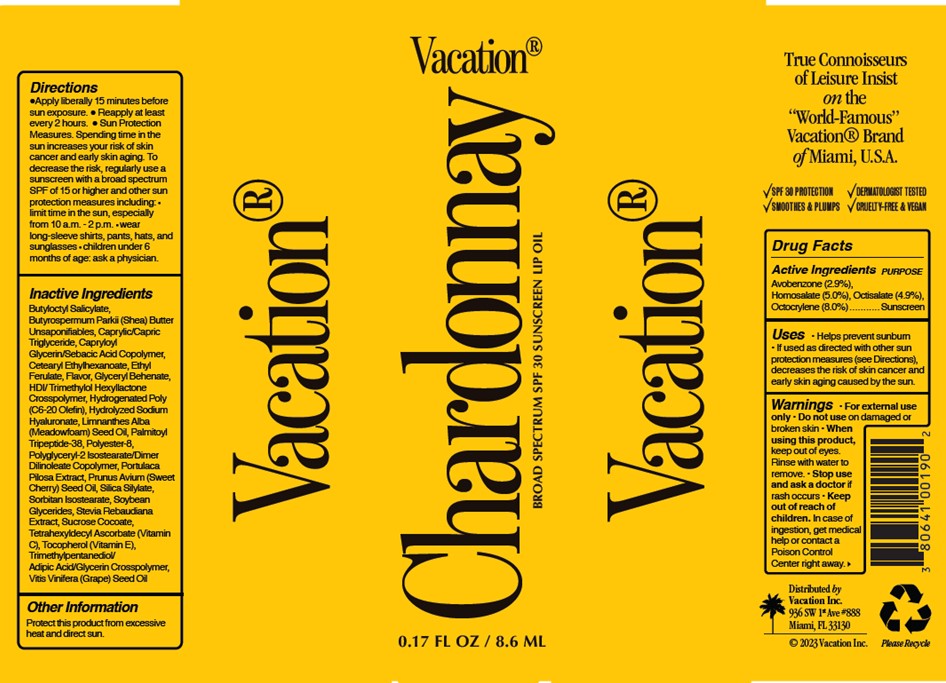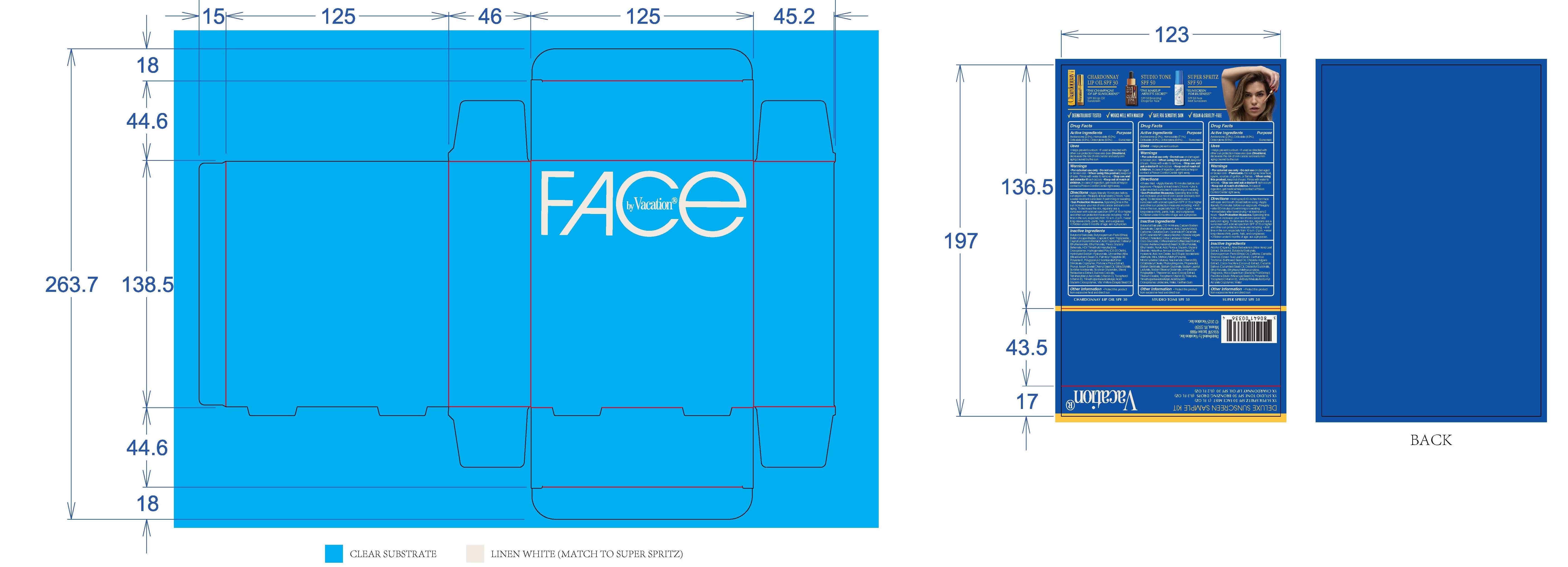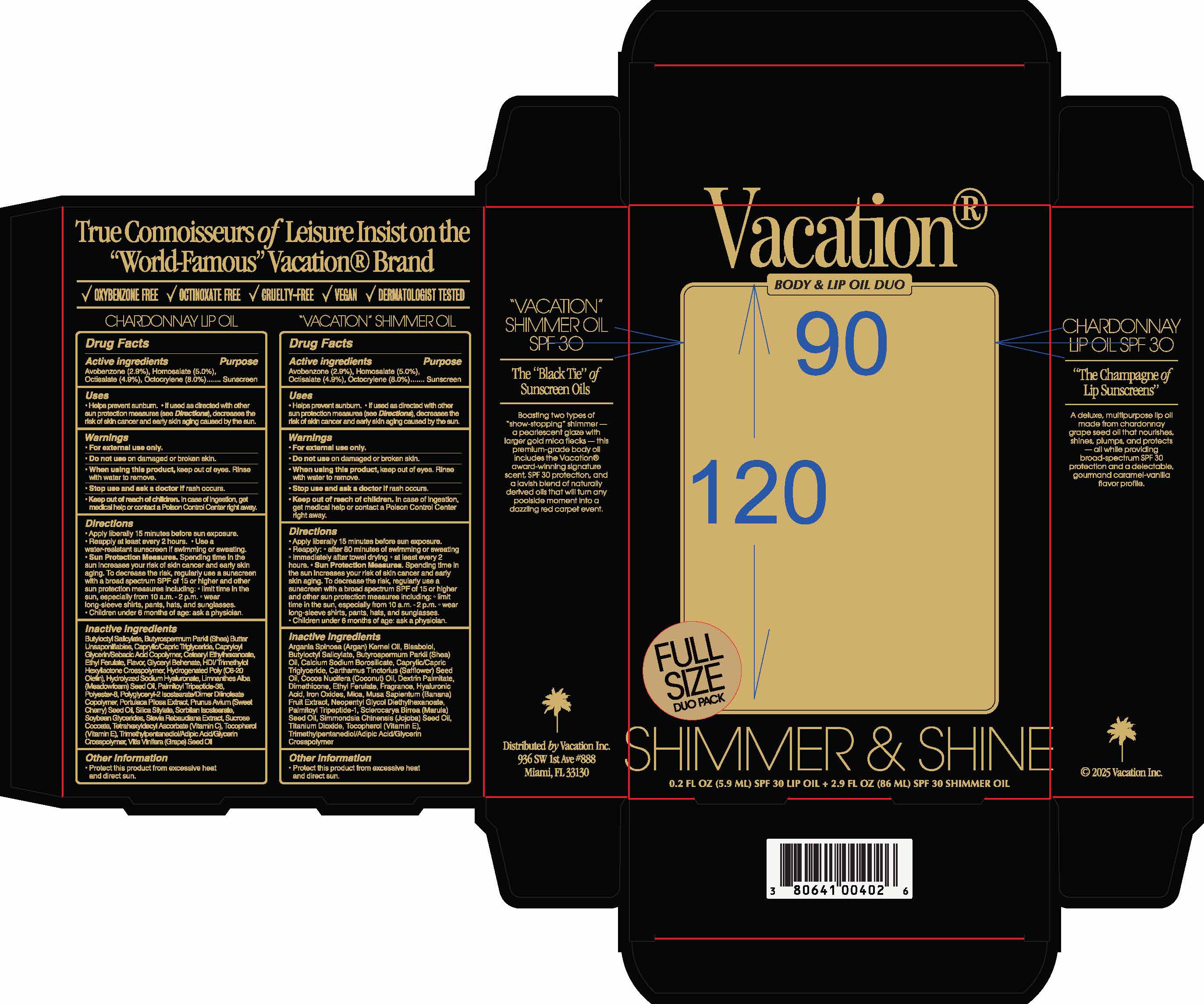 DRUG LABEL: Chardonnay Lip Oil
NDC: 80641-012 | Form: OIL
Manufacturer: Vacation Inc
Category: otc | Type: HUMAN OTC DRUG LABEL
Date: 20250418

ACTIVE INGREDIENTS: OCTOCRYLENE 8 g/100 mL; AVOBENZONE 2.9 g/100 mL; OCTISALATE 4.9 g/100 mL; HOMOSALATE 5 g/100 mL
INACTIVE INGREDIENTS: BUTYLOCTYL SALICYLATE

Vacation Chardonnay SPF 30 Lip Oil

Dosage and Administration

For external use only

Warnings

For external use only

Do not use on damaged or broken skin

When using this product, keep out of eyes. Rinse with water to remove

Stop use and ask a doctor if rash occurs

Indications and Usage

Helps prevent sunburn

If used as directed with other sun protection measures (see Directions), decreases the risk of skin cancer and early skin aging caused by the sun

Keep out of reach of children

Purpose

Sunscreen

Inactives

Butyloctyl Salicylate, Butyrospermum Parkii (Shea) Butter, Caprylic/Capric Triglyceride, Capryloyl Glycerin/Sebacic Acid Copolymer, Cetearly Ethylhexanoate, Ethyl Ferulate, Flavor, Glyceryl, Behenate, HDI/Trimethylol Hexyllactone Crosspolymer, Hydrogenated Poly (C6-20 Olefin), Hydrolyzed Sodium Hyaluyronate, Limnanthes Alba (Meadowfoam) Seed Oil, Palmitoyl Tripeptide-38, Polyester-8, Polyglyceryl-2 Isostearate/Dimer Dilinoleate Copolymer, Portulaca Pilosa Extract, Prunus Avium (Sweet Cherry) Seed Oil, Silica Silylate, Sorbitan Isostearate, Soybean Glycerides, Stevia Rebaudiana Extract, Sucrose Cocoate, Tetrahexyldecyl Ascorbate (Vitamin C), Tocopherol (Vitamin E), Trimethylpentanediol/Adipic Acid/Glycerin Crosspolymer, Vitis Vinifera (Grape) Seed Oil